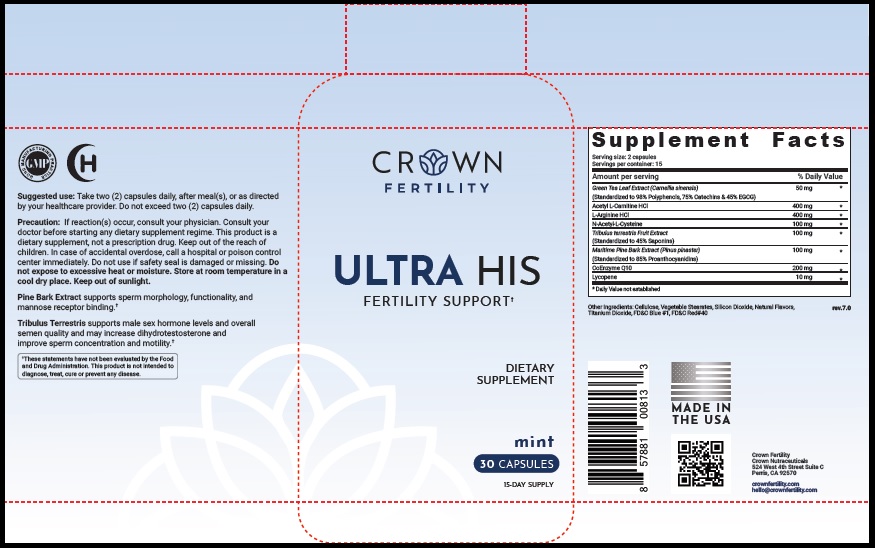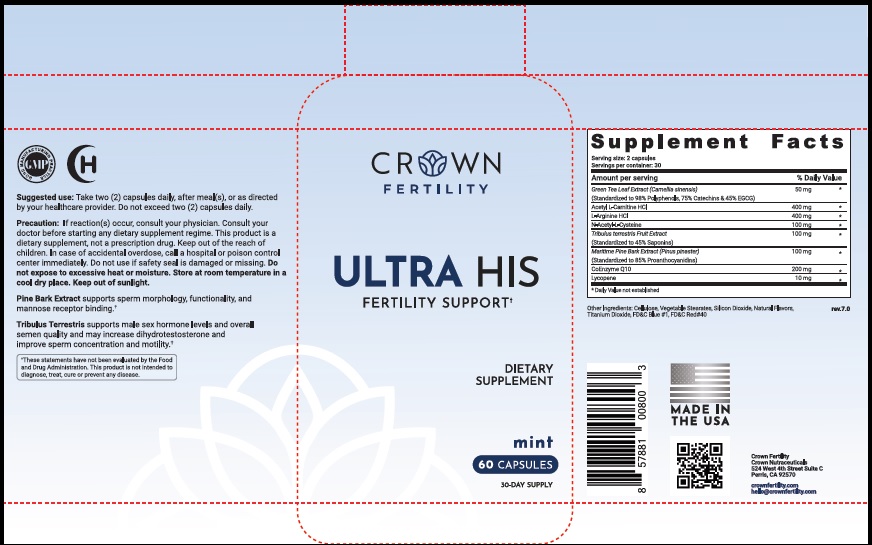 DRUG LABEL: ULTRA HIS MINT
NDC: 73489-005 | Form: CAPSULE
Manufacturer: CROWN GENERAL AGENCY INC
Category: other | Type: Dietary Supplement
Date: 20211022

ACTIVE INGREDIENTS: GREEN TEA LEAF 50 mg/1 1; ACETYLCARNITINE HYDROCHLORIDE 400 mg/1 1; ARGININE HYDROCHLORIDE 400 mg/1 1; N-MONOACETYLCYSTINE 100 mg/1 1; TRIBULUS TERRESTRIS FRUIT 100 mg/1 1; MARITIME PINE 100 mg/1 1; UBIDECARENONE 200 mg/1 1; LYCOPENE 10 mg/1 1
INACTIVE INGREDIENTS: POWDERED CELLULOSE; MAGNESIUM STEARATE; SILICON DIOXIDE; TITANIUM DIOXIDE; FD&C BLUE NO. 1; FD&C RED NO. 40

STATEMENT OF IDENTITY

Dietary Supplement

Suggested Use

Take two (2) capsules daily, after meal(s), or as directed by your healthcare provider. Do not exceed two (2) capsules daily.

Precaution

If reaction(s) occur, consult your physician. Consult your doctor before starting any dietary supplement regime. This product is a dietary supplement, not a prescription drug. Keep out of the reach of children. In case of accidental overdose, call a hospital or poison control center immediately. Do not use if safety seal is damaged or missing. Do not expose to excessive heat or moisture. Store at room temperature in a cool dry place. Keep out of sunlight.